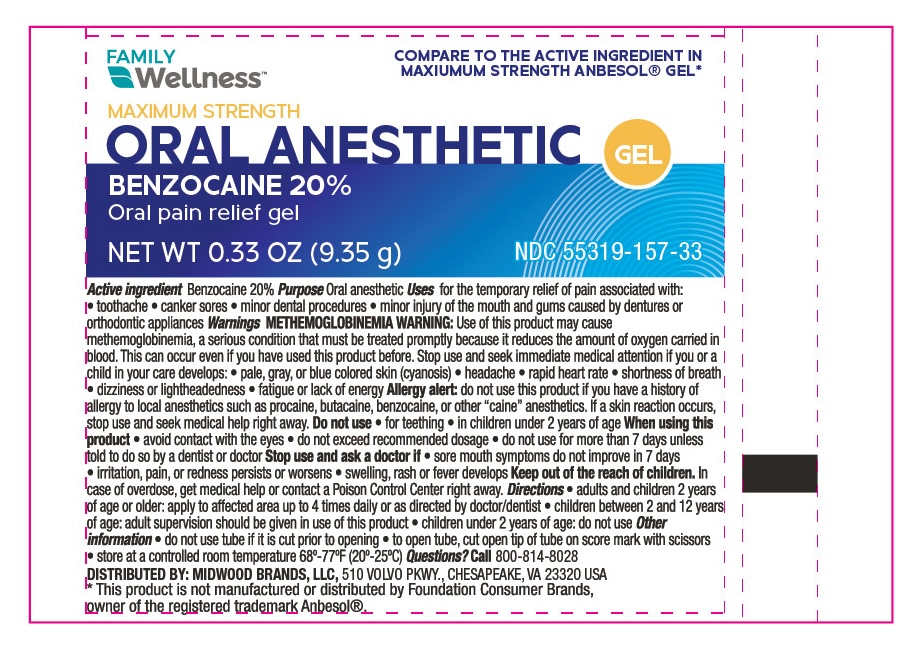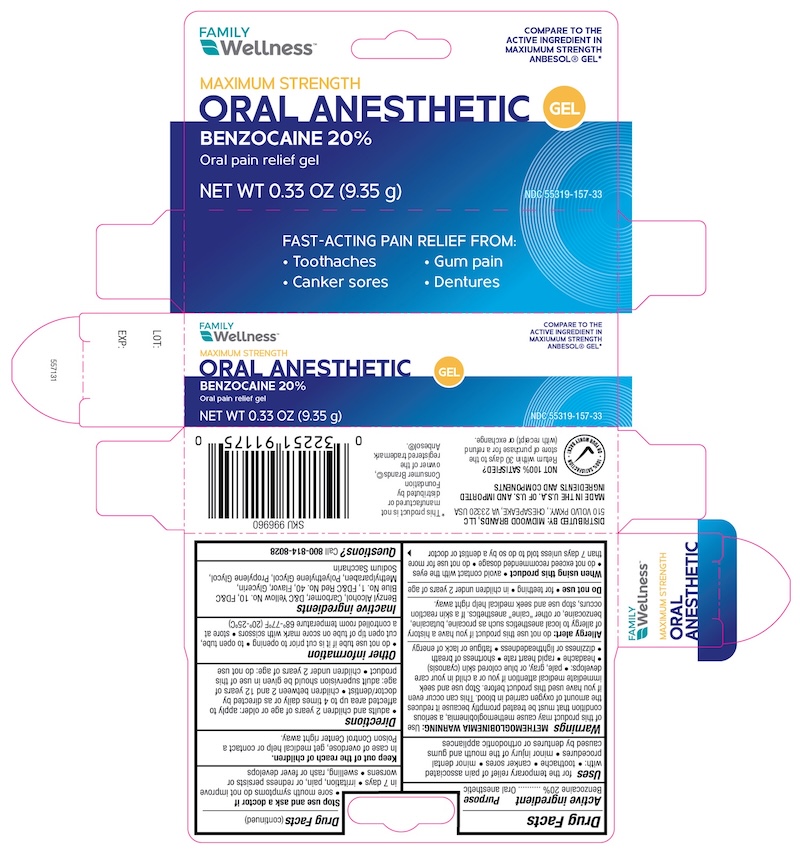 DRUG LABEL: Family Wellness Pain Relief
NDC: 55319-157 | Form: GEL
Manufacturer: FAMILY DOLLAR (Family Wellness)
Category: otc | Type: HUMAN OTC DRUG LABEL
Date: 20260121

ACTIVE INGREDIENTS: BENZOCAINE 200 mg/1 g
INACTIVE INGREDIENTS: BENZYL ALCOHOL; CARBOMER 940; D&C YELLOW NO. 10; FD&C RED NO. 40; GLYCERIN; METHYLPARABEN; POLYETHYLENE GLYCOL 3350; PROPYLENE GLYCOL; SODIUM SACCHARIN

Family Wellness Oral Pain Relief

Active Ingredient

Benzocaine 20%

Purpose

Oral Pain Reliever

Uses

- temporary relief of occasional minor irritation, pain and sore mouth

Warnings

Methemoglobinema Warning:Use of this product may cause Methemoglobinema, a serious condition that must be treated promptly becasue it reduces the amount of oxygem carried in the blood. This can occur even if you have used this product before. Stop use and seek immeditate medical attention if you or a child in yuor care develops;

- pale, gray, or blue colored skin(cyanosis)
- headache
- rapid heart rate
- shortness of breath
- dizziness or lightheadedness
- fatigue or lack of energy

Allergy alert:Do not use this product if you have a history of allergy to local anesthetics such as procaine, butacaine, benzocaine or other "caine" anesthetics.

Do not use

more than directed
for more than 7 days unless told to do so by a dentist or doctor

Stop use and ask a Doctor if

swelling, rash or fever develops
irritation, pain, or redness persists or worsens

Keep out of reach of children.In case of overdose, get medical help or contact a Poison Control Center right away.

Directions

- do not use tube if it is cut prior to opening
- cut open tip of tube on score mark
- use your fingertip or cotton applicator to apply a small pea-size amount of Oral Pain Relief Gel
- apply to affected area up to four times daily or as directed by a dentist or physician
- Adults and children 2 years of age and older: Apply to affected area
- Children under 12 years of age should be supervised in the use of this product
- Children under 2 years of age: Consult a doctor

Inactive Ingredients

Benzyl Alcohol, Carbomer, D&C Yellow No 10, FD&C Blue No 1, FD&C Red No 40, Flavor, Glycerin, Methylparaben, Polyethylene Glycol, Propylene Glycol, Sodium Saccharin

Other information

store at a controlled room temperature 68°- 77°F (20°-25°C)

Principal Display Panel

NDC 55319-157-33

Family Wellness

Oral Pain Relief

MAXIMUM STRENGTH GEL

Benzocaine 20% NET WT. 0.33 OZ (9.35g)